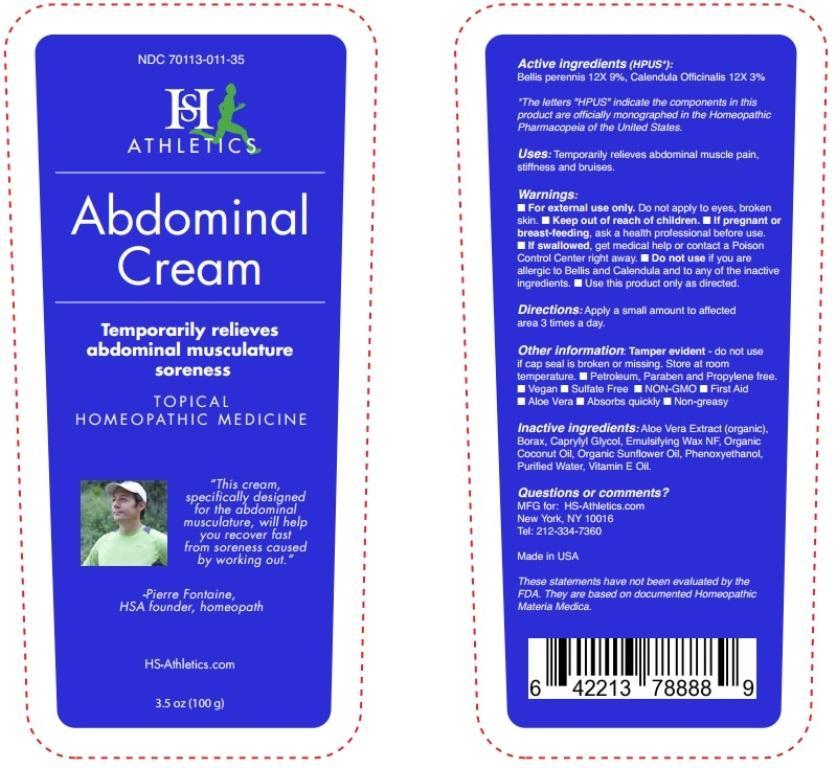 DRUG LABEL: Abdominal Cream
NDC: 70113-011 | Form: CREAM
Manufacturer: Homeopathic Services Inc. 
Category: homeopathic | Type: HUMAN OTC DRUG LABEL
Date: 20190905

ACTIVE INGREDIENTS: BELLIS PERENNIS 12 [hp_X]/1 g; CALENDULA OFFICINALIS FLOWERING TOP 12 [hp_X]/1 g
INACTIVE INGREDIENTS: ALOE VERA LEAF; SODIUM BORATE; CAPRYLYL GLYCOL; POLYSORBATE 60; CETOSTEARYL ALCOHOL; PEG-150 STEARATE; STEARETH-20; COCONUT OIL; SUNFLOWER OIL; PHENOXYETHANOL; WATER; .ALPHA.-TOCOPHEROL

Abdominal Cream

Active ingredients (HPUS*):

Bellis perennis 12X 9%, Calendula Officinalis 12X 3%

*The letters "HPUS" indicate the components in this product are officially monographed in the Homeopathic Pharmacopeia of the United States.

INDICATIONS AND USAGE

Uses: Tempoarily relieves abdominal muscle pain, stiffness and bruises.

These statements have not been evaluated by the FDA. They are based on documented Homeopathic Materia Medica.

Warnings:

- For external use only. Do not apply to eyes, broken skin.
- If pregnant or breast-feeding, ask a health professional before use.
- If swallowed, get medical help or contact a Poison Control Center right away.
- Do not use if you are allergic to Bellis and Calendula and to any of the inactive ingredients.
- Use this product only as directed.

- Keep out of reach of children.

DOSAGE AND ADMINISTRATION

Directions: Apply a small amount to affected area 3 times a day.

Other information: Tamper evident - do not use if cap seal is broken or missing. Store at room temperature.

- Petroleum, paraben, propylene free
- Vegan
- Sulfate free
- NON-GMO
- First Aid
- Aloe Vera
- Absorbs quickly
- Non-greasy

INACTIVE INGREDIENT

Inactive ingredients: Aloe Vera Extract (organic), Borax, Caprylyl Glycol, Emulsifying Wax NF, Organic Coconut Oil, Organic Sunflower Oil, Phenoxyethanol, Purified Water, Vitamin E Oil.

Questions or comments?

MFG for: HS-Athletics.com

New York, NY 10016

Tel: 212-334-7360

PACKAGE LABEL

NDC 70113-011-35

HS Athletics

Abdominal Cream

Temporarily relieves adbdominal musculature soreness

TOPICAL HOMEOPATHIC MEDICINE

"This cream specifically designed for the adbdominal musculature, will help y ou recover fast from soreness caused by working out."

-Pierre Fontaine,

HSA founder, homeopath

HS-Athletics.com

3.5 oz (100g)

PURPOSE

Temporarily relieves abdominal musculature soreness